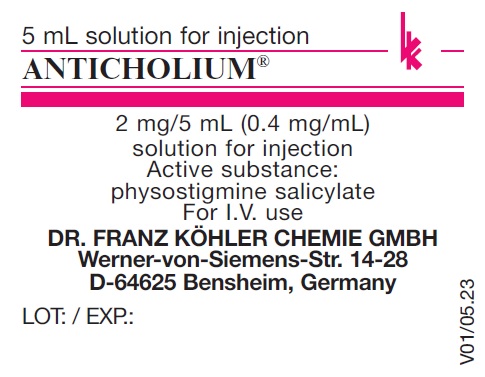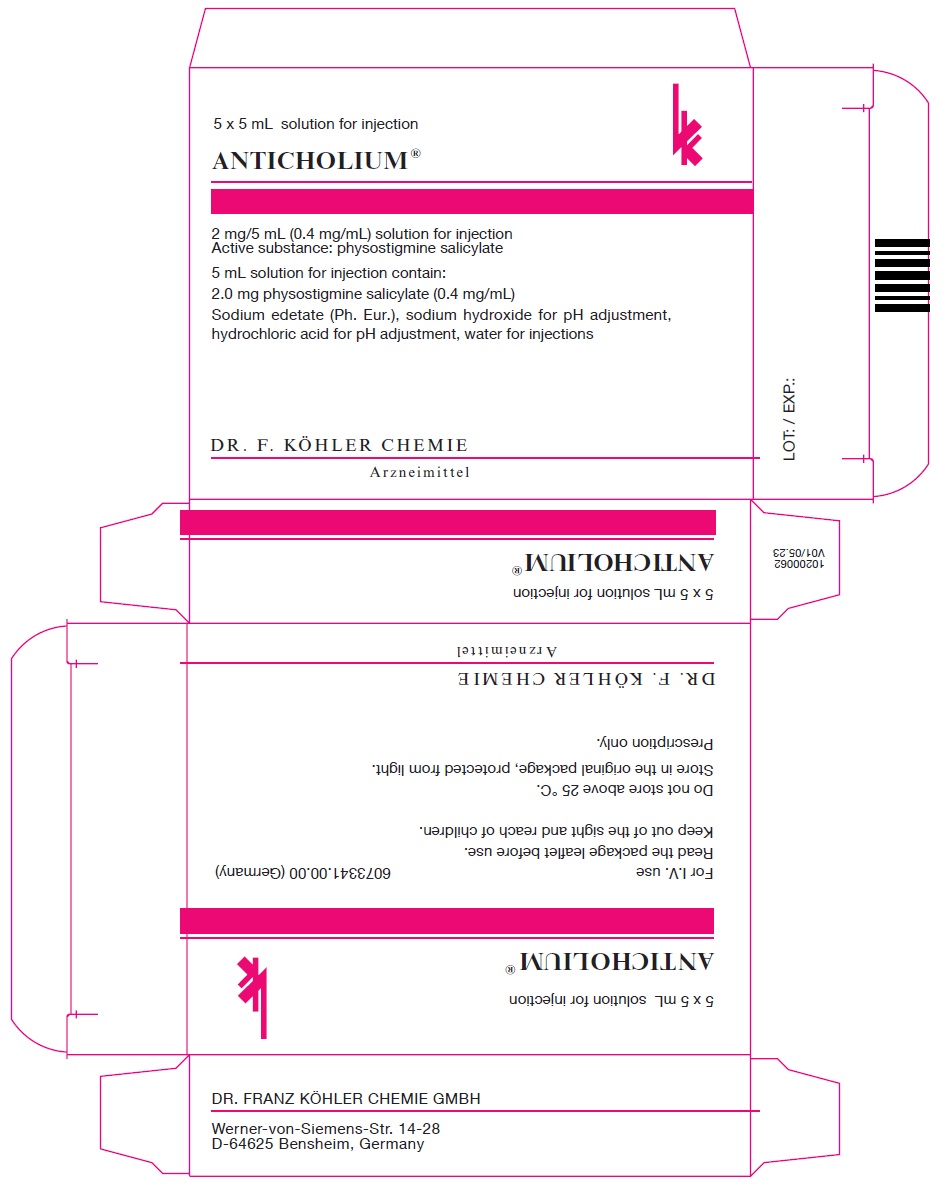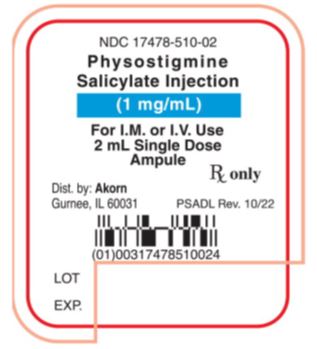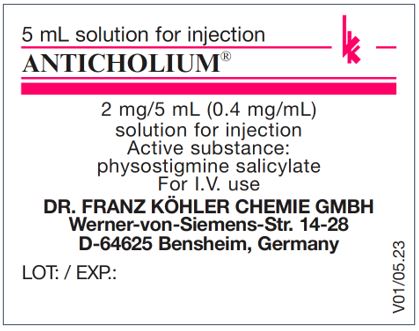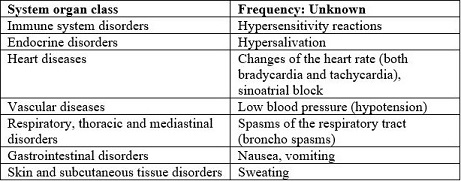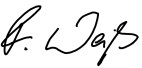 DRUG LABEL: ANTICHOLIUM
NDC: 81284-831 | Form: INJECTION
Manufacturer: Provepharm Inc.
Category: prescription | Type: HUMAN PRESCRIPTION DRUG LABEL
Date: 20251111

ACTIVE INGREDIENTS: PHYSOSTIGMINE SALICYLATE 0.4 mg/1 mL
INACTIVE INGREDIENTS: EDETATE SODIUM; SODIUM HYDROXIDE; HYDROCHLORIC ACID; WATER

ANTICHOLIUM®
solution for injection or infusion

HEALTH CARE PROVIDER LETTER

September 2023

IMPORTANT PRESCRIBING INFORMATION

Subject:

Temporary Importation of Anticholium® (physostigmine salicylate) Ampules with Foreign, non-U.S. Labeling to Address Supply Shortage

Dear Healthcare Provider,

To address the ongoing shortages of physostigmine salicylate injection in the United States, Dr. Franz Köhler Chemie GmbH (Koehler) in conjunction with Provepharm Inc. (Provepharm) and Direct Success, Inc. (Direct Success) is coordinating with the U.S. Food and Drug Administration (FDA) to temporarily import Anticholium® (Physostigmine salicylate, 2mg/5ml, injection solution for intravenous use) into the U.S. market. Koehler’s Anticholium® (Physostigmine salicylate, 2mg/5ml, injection solution for intravenous use), marketed and manufactured in Germany for Koehler, is not FDA-approved.

At this time, no other entity except Provepharm or its distributor Direct Success is authorized by the FDA to import or distribute physostigmine salicylate injection in the U.S.

Effective immediately, Provepharm will distribute the following presentations of Anticholium® (physostigmine salicylate) to address the critical shortage:

Product Description | Strength | Packaging | NDC number | Lot/; Batch # | Expiration Date; (Labeled)
Anticholium® (physostigmine salicylate) | 2 mg/5 mL (0.4 mg/mL) injection for intravenous use | 5 x 5 mL ampules | 81284-831-05 | 2315751 | 2026-05-31

To place an order, please contact Direct Success at Distribution@DSuccess.com or 1-877-404-3338.

The U.S. imported Anticholium (physostigmine salicylate) injection contains nitrogen even though it is not listed on the enclosed Instructions for Use (IFU).

The barcode on the imported product label may not register accurately on the U.S. scanning systems. Institutions should manually input the imported product information into their systems and confirm that the barcode, if scanned, provides correct information. Alternative procedures should be followed to assure that the correct drug product is being used and administered to individual patients.

In addition, the packaging of the imported product does not include serialization information. Koehler’s Anticholium® does not meet the Drug Supply Chain Security Act (DSCSA) requirements for the Interoperable Exchange of Information for Tracing of Human, Finished Prescription Drugs.

There are key differences between the U.S. marketed physostigmine salicylate injection and ANTICHOLIUM® noted in Table 1 below.

Table 1. Key Differences between physostigmine salicylate injection and Anticholium®
Product Names | U.S. physostigmine salicylate injection | Anticholium®; (German imported product)
Indication | To reverse the effect upon the central nervous system, caused by clinical or toxic dosages of drugs capable of producing the anticholinergic syndrome. | Indicated for central anticholinergic syndrome (CAS), delayed postoperative awakening and shivering; Indicated as an antidote and/or antagonist in case of intoxication with and/or overdose of: alcohol, tropane alkaloids, amanita pantherina and amanita muscaria, tricyclic antidepressants, antiemetics/antihistamines, neuroleptic drugs, benzodiazepines, antispasmodics, parkinson disease medication, baclofen, 4-hydroxybutyric acid (GHB), inhalation anesthetics, ketamine, 3-quinuclidinyl benzilate
Administration | Injection for intramuscular or intravenous use | Injection solution for intravenous use only
Packaging | 2 mL in 1 AMPULE | 5 ampules of 5 ml containing 2 mg of physostigmine salicylate

When using Anticholium® (Physostigmine) from Koehler the following advice has to be taken into account:

Dosing and administration:

For the treatment of postoperative awakening disorders in adults:

Slowly inject physostigmine intravenously at a dose of 0.04 mg/kg body weight (approx. 1 mg/min), the maximum individual dose is 2 mg. In case of insufficient effect, give subsequent injections after 5 to 20 minutes at the earliest, after a positive evaluation of the effect of the first injection.

Treatment in cases of intoxication:

Adults: Slowly inject 0.04 mg/kg body weight (2 mg) of physostigmine salicylate intravenously and subsequently inject 1-4 mg every 20 minutes. Repeat the effective dose if the intoxication symptoms recur, also in the form of a continuous infusion if deemed useful.

Children and adolescents: Infants: Start with a low dose of 0.5 mg of physostigmine salicylate administered intravenously, repeat this dose every 5 minutes up to the overall dose of 2 mg, as long as the toxic, anticholinergic symptoms continue to persist and no cholinergic symptoms occur.

Method of administration:

Anticholium® should be administered intravenously slowly or as brief infusion in 50 ml physiological saline solution over 10-15 minutes. A general criterion for adequate physostigmine dosing is the recognizable recovery of mental abilities and responsiveness (e.g. specifying name, address, date).

For further Information please refer to the full prescribing information enclosed.

Prescription and Labeling:

Anticholium® will be available only by prescription in the U.S. However, the imported product does not have the statement “Rx only” on the labeling.

There is no barcode on this product for use with U.S. barcode scanning systems. Alternative procedures should be followed to ensure that the correct drug product is being used and administered to individual patients.

Reporting Adverse Events:

Healthcare providers should report adverse events associated with the use of Koehler’s Anticholium® to Provepharm at:

Phone: 1-833-727-6556

email: safety-us@provepharm.com

Adverse reactions or quality problems experienced with the use of this product may be reported to the FDA’s MedWatch Adverse Event Reporting program either online, by regular mail or by fax.

- Complete and submit the report Online: www.fda.gov/medwatch/report.htm

- Regular Mail or Fax: Download form https://www.accessdata.fda.gov/scripts/medwatch/index.cfm or call 1-800-332-1088 to request a reporting form, then complete and return to the address on the pre-addressed form, or submit by fax to 1-800-FDA-0178 (1-800-332-0178).

You may also contact our medical information department at medicalaffairs@provepharm.com if you have any questions about the information contained in this letter or the safe and effective use of Anticholium®.

This letter is not intended as a complete description of the benefits and risks related to the use of Anticholium®. Please refer to the enclosed full prescribing information.

For additional information, please contact Dr. Franz Köhler Chemie GmbH at info@koehler-chemie.de or visit www.koehler-chemie.de

Finally, please ensure that your staff and others in your institution who may be involved in the administration of Anticholium® receive a copy of this letter and review the information.

Sincerely,

Frauke Weiß
CEO

Enclosure: Anticholium®Full Prescribing Information

 | US Product | Import Product
Product name | Physostigmine Salicylate Injection | ANTICHOLIUM®
Disclaimer | Disclaimer: This drug has not been found by FDA to be safe and effective, and this labeling has not been approved by FDA. For further information about unapproved drugs, click here. | Disclaimer: Anticholium® (physostigmine salicylate) is not FDA approved, but is imported with foreign, non-U.S. labeling under a temporary importation license to address supply shortage.
Dosage Form | solution for injection | solution for injection or infusion
Label
Composition | Physostigmine Salicylate Injection is available in 2 mL ampules, each mL containing 1 mg of Physostigmine Salicylate in a vehicle composed of sodium metabisulfite 0.1%, benzyl alcohol 2.0% as a preservative in Water for Injection. | Anticholium® is available in 5 mL ampules, each mL containing 0.4 mg physostigmine salicylate in a vehicle composed of sodium edetate (Ph. Eur.), nitrogene and water for injection.
Indications | INDICATIONS AND USAGE:; To reverse the effect upon the central nervous system, caused by clinical or toxic dosages of drugs capable of producing the anticholinergic syndrome . | Anticholium® is indicated for:; 1. the use as an antidote and/or antagonist in case of intoxication with and/or overdose of:; - alcohol - tropane alkaloids (hyoscyamine, atropine, scopolamine, as e.g. in brugmansia, datura, atropa belladonna) - amanita pantherina and amanita muscaria - tricyclic antidepressants (amitriptyline, imipramine, trimipramine, clomipramine, doxepine) - antiemetics/antihistamines (phenothiazine, thioridazine, chlorpromazine, promethazine, diphenhydramine, dimenhydrinate) - neuroleptic drugs (especially butyrophenones) - benzodiazepines - tolterodine, oxybutynine - amantadine, diphenhydramine - baclofen - 4-hydroxybutyric acid (GHB) - inhalation anesthetics - ketamine - 3-quinuclidinyl benzilate; 2. the treatment of postoperative disorders:; - Central anticholinergic syndrome (CAS) - Delayed postoperative awakening - Shivering
Contraindications | Physostigmine Salicylate Injection should not be used in the presence of asthma, gangrene, diabetes, cardiovascular disease, mechanical obstruction of the intestine or urogenital tract or any vagotonic state, and in patients receiving choline esters and depolarizing neuromuscular blocking agents (decamethonium, succinylcholine).; For post-anesthesia, the concomitant use of atropine with physostigmine salicylate is not recommended, since the atropine antagonizes the action of physostigmine. | Anticholium® should not be used in the presence of hypersensitivity to physostigmine salicylate, bronchial asthma, ulcers associated with tissue destruction (gangrene), coronary heart disease, constipation (mechanical obstipation), mechanical ischuria (urinary retention), hereditary form of muscle atrophy (myotonic dystrophy), closed traumatic brain injuries, intestinal obstruction, spasms in the urinary tract collection system, inactivation of nerve and muscle cells after administration of drugs to relax the muscles (depolarization block after depolarizing muscle relaxants), in case of intoxication due to “irreversibly acting” cholinesterase inhibitors (drugs used to treat dementia), intoxication with phosphoric acid esters or barbiturates.
Precautions | PRECAUTIONS:; Because of the possibility of hypersensitivity in an occasional patient, atropine sulfate injection should always be at hand since it is an antagonist and antidote for physostigmine. | Talk to your doctor before you are given Anticholium® if you suffer from diabetes mellitus, slowed heart rate (bradycardia), disturbances of the atrioventricular conduction system, Parkinson’s disease or ulcerative colitis.; Hypersensitivity reactions may occur after administration of this medicine. These reactions may vary individually and may also cause life-threatening conditions. It is recommended to have emergency medication and medical aids ready. A risk/benefit analysis should be performed, and discontinuation of treatment should be considered.; Acute cardiac arrest may be possible during treatment with tricyclic antidepressants; therefore, Anticholium® should only be considered as an antidote for this indication while the patient has continuous ECG monitoring.
Interactions | - | Tell your doctor or pharmacist if you are taking/using, have recently taken/used or intend to take/use any other medicines.; In case of simultaneous administration of other cholinesterase inhibitors (e.g. medicines for the treatment of dementia), caution should be exercised because of the potentiating effect. In intoxication with depolarizing muscle relaxants of the suxamethonium type, Anticholium® is contraindicated!
Warnings | Contains sodium bisulfite, a sulfite that may cause allergic-type reactions including anaphylactic symptoms and life-threatening or less severe asthmatic episodes in certain susceptible people. The overall prevalence of sulfite sensitivity in the general population is unknown and probably low. Sulfite sensitivity is seen more frequently in asthmatic than in non-asthmatic people.; If excessive symptoms of salivation, emesis, urination and defecation occur, the use of Physostigmine Salicylate Injection should be terminated. If excessive sweating or nausea occur, the dosage should be reduced.; Intravenous administration should be at a slow, controlled rate, no more than 1 mg per minute (see dosage). Rapid administration can cause bradycardia, hypersalivation leading to a respiratory difficulties and possible convulsions.; An overdosage of Physostigmine Salicylate Injection can cause a cholinergic crisis. | Talk to your doctor before you are given Anticholium® if you suffer from diabetes mellitus, slowed heart rate (bradycardia), disturbances of the atrioventricular conduction system, Parkinson’s disease or ulcerative colitis.; Hypersensitivity reactions may occur after administration of this medicine. These reactions may vary individually and may also cause life-threatening conditions. It is recommended to have emergency medication and medical aids ready. A risk/benefit analysis should be performed and discontinuation of treatment should be considered.; Acute cardiac arrest may be possible during treatment with tricyclic antidepressants; therefore, Anticholium® should only be considered as an antidote for this indication while the patient has continuous ECG monitoring.
Dosage and Administration | Past Anesthesia Care: 0.5 to 1.0 mg intramuscularly or intravenously. INTRAVENOUS ADMINISTRATION SHOULD BE AT A SLOW CONTROLLED RATE OF NO MORE THAN 1 MG PER MINUTE. Dosage may be repeated at intervals of 10 to 30 minutes if desired patient response is not obtained.; PEDIATRIC DOSAGE:; Recommended dosage is 0.02 mg/kg; intramuscularly or by slow intravenous injection, no more than 0.5 mg per minute. If the toxic effects persist, and there is no sign of cholinergic effects, the dosage may be repeated at 5 to 10 minute intervals until a therapeutic effect is obtained or a maximum of 2 mg dosage is attained.; IN ALL CASES OF POISONING, THE USUAL SUPPORTIVE MEASURES SHOULD BE UNDERTAKEN. | Use in adults:; For the treatment of postoperative awakening disorders:; Slowly inject physostigmine intravenously at a dose of 0.04 mg/kg bodyweight (approx. 1 mg/min), the maximum individual dose is 2 mg.; In case of insufficient effect, give subsequent injections after 5 to 20 minutes at the earliest, after a positive evaluation of the effect of the first injection.; In cases of intoxication:; Adults: Slowly inject 0.04 mg/kg bodyweight (2 mg) of physostigmine salicylate intravenously and subsequently inject 1-4 mg every 20 minutes. Repeat the effective dose if the intoxication symptoms recur, also in the form of a continuous infusion if deemed useful.; Use in children and adolescents:; In cases of intoxication:; Infants: Start with a low dose of 0.5 mg of physostigmine salicylate administered intravenously, repeat this dose every 5 minutes up to the overall dose of 2 mg, as long as the toxic, anticholinergic symptoms continue to persist, and no cholinergic symptoms occur.; Method of administration; Intravenously slowly or as brief infusion in 50 ml physiological saline solution over 10-15 minutes. A general criterion for adequate physostigmine dosing is the recognizable recovery of mental abilities and responsiveness (e.g. specifying name, address, date).
Overdosage | Can cause a cholinergic crisis. Appropriate antidote is atropine sulfate. | Intravenous administration of atropine up to normalization of the symptoms.; Normally, half the amount of the administered physostigmine salicylate is sufficient. In case of intoxication, measures to prevent absorption are to be started immediately (such as gastric lavage, administration of medicinal charcoal and laxatives).; The following information is intended for healthcare professionals:; Overdose emergency measures, symptoms, antidotes; In cases of intoxication, measures to prevent absorption such as gastric lavage, administration of medicinal charcoal and laxatives are to be started immediately.; An overdose of Anticholium® can cause bradycardia, hypersalivation, vomiting, and generalized tonic-clonic seizures.; Patients should be closely monitored by ECG.
Adverse Reactions | Nausea, vomiting and salivation; can be offset by reducing dosage. Bradycardia and convulsions, if intravenous administration is too rapid. See DOSAGE AND ADMINISTRATION. | Like all medicines, Anticholium® can cause side effects, although not everybody gets them.
Usage in pregnancy | Safe use in pregnancy and lactation has not been established; therefore, use in pregnant women, nursing mothers or women who may become pregnant requires that possible benefits be weighed against possible hazards to mother and child. | Pregnancy and breast-feeding Pregnancy:; There is no experience with the use of Anticholium® in pregnant women.; Physostigmine, the active substance contained in Anticholium®, passes into the placenta. Animal studies are insufficient with respect to effects on pregnancy, embryonal/foetal development, birth and postnatal development. The potential risk for humans is unknown.; For this reason, Anticholium® may only be administered to pregnant women if deemed absolutely necessary by the attending doctor.; Breast-feeding:; There is no experience with the use of Anticholium® during breastfeeding.; It is not known whether physostigmine, the active substance contained in Anticholium®, is excreted in human breast milk. For this reason, Anticholium® may only be used during breastfeeding if deemed absolutely necessary by the attending doctor.
Storage Conditions | STORAGE: Store at 20° to 25°C (68° to 77°F) [see USP Controlled Room Temperature]. | Store this medicine protected from light in the outer packaging, not above 25°C.; In undamaged container: 3 years The infusion solution should be used immediately after preparation.; Keep this medicine out of the reach of children.; Do not use this medicine after the expiry date which is stated on the carton/label after EXP. The expiry date refers to the last day of that month.
How Supplied | NDC 17478-510-02; 2 mL Ampules packed 10 per box, 1 mg per mL. | Anticholium® is a clear, colorless to slightly reddish solution in glass ampules.; Pack containing 5 ampules with 5 ml.

Composition:

Anticholium is available in 5 mL ampules, each mL containing 0.4 mg physostigmine salicylate in a vehicle composed of sodium edetate (Ph. Eur.) and water for injection.

Indications:

ANTICHOLIUM® is indicated for:
1. the use as an antidote and/or antagonist in case of intoxication with and/or overdose of:

- alcohol
- tropane alkaloids (hyoscyamine, atropine, scopolamine, as e.g. in brugmansia, datura, atropa belladonna)
- amanita pantherina and amanita muscaria
- tricyclic antidepressants (amitriptyline, imipramine, trimipramine, clomipramine, doxepine)
- antiemetics/antihistamines (phenothiazine, thioridazine, chlorpromazine, promethazine, diphenhydramine, dimenhydrinate)
- neuroleptic drugs (especially butyrophenones)
- benzodiazepines
- tolterodine, oxybutynine
- amantadine, diphenhydramine
- baclofen
- 4-hydroxybutyric acid (GHB)
- inhalation anesthetics
- ketamine
- 3-quinuclidinyl benzilate

2. the treatment of postoperative disorders:

- Central anticholinergic syndrome (CAS)
- Delayed postoperative awakening
- Shivering

Contraindications:

ANTICHOLIUM® should not be used in the presence of hypersensitivity to physostigmine salicylate, bronchial asthma, ulcers associated with tissue destruction (gangrene), coronary heart disease, constipation (mechanical obstipation), mechanical ischuria (urinary retention), hereditary form of muscle atrophy (myotonic dystrophy), closed traumatic brain injuries, intestinal obstruction, spasms in the urinary tract collection system, inactivation of nerve and muscle cells after administration of drugs to relax the muscles (depolarization block after depolarizing muscle relaxants), in case of intoxication due to “irreversibly acting” cholinesterase inhibitors (drugs used to treat dementia), intoxication with phosphoric acid esters or barbiturates.

Precautions:

Talk to your doctor before you are given ANTICHOLIUM® if you suffer from diabetes mellitus, slowed heart rate (bradycardia), disturbances of the atrioventricular conduction system, Parkinson’s disease or ulcerative colitis.

Hypersensitivity reactions may occur after administration of this medicine. These reactions may vary individually and may also cause life-threatening conditions. It is recommended to have emergency medication and medical aids ready. A risk/benefit analysis should be performed, and discontinuation of treatment should be considered.

Acute cardiac arrest may be possible during treatment with tricyclic antidepressants; therefore, Anticholium should only be considered as an antidote for this indication while the patient has continuous ECG monitoring.

Interactions:

Tell your doctor or pharmacist if you are taking/ using, have recently taken/used or intend to take/ use any other medicines.

In case of simultaneous administration of other cholinesterase inhibitors (e.g. medicines for the treatment of dementia), caution should be exercised because of the potentiating effect. In intoxication with depolarizing muscle relaxants of the suxamethonium type, ANTICHOLIUM® is contraindicated!

Dosage and Administration:

Use in adults:

For the treatment of postoperative awakening disorders:

Slowly inject physostigmine intravenously at a dose of 0.04 mg/kg bodyweight (approx. 1 mg/min), the maximum individual dose is 2 mg.
In case of insufficient effect, give subsequent injections after 5 to 20 minutes at the earliest, after a positive evaluation of the effect of the first injection.

In cases of intoxication:

Adults: Slowly inject 0.04 mg/kg bodyweight (2 mg) of physostigmine salicylate intravenously and subsequently inject 1-4 mg every 20 minutes. Repeat the effective dose if the intoxication symptoms recur, also in the form of a continuous infusion if deemed useful.

Use in children and adolescents:

In cases of intoxication:

Infants: Start with a low dose of 0.5 mg of physostigmine salicylate administered intravenously, repeat this dose every 5 minutes up to the overall dose of 2 mg, as long as the toxic, anticholinergic symptoms continue to persist, and no cholinergic symptoms occur.

Method of administration:

Intravenously slowly or as brief infusion in 50 ml physiological saline solution over 10-15 minutes. A general criterion for adequate physostigmine dosing is the recognizable recovery of mental abilities and responsiveness (e.g. specifying name, address, date).

Overdosage:

Intravenous administration of atropine up to normalization of the symptoms.

Normally, half the amount of the administered physostigmine salicylate is sufficient. In case of intoxication, measures to prevent absorption are to be started immediately (such as gastric lavage, administration of medicinal charcoal and laxatives).

The following information is intended for healthcare professionals:

Overdose emergency measures, symptoms, antidotes

In cases of intoxication, measures to prevent absorption such as gastric lavage, administration of medicinal charcoal and laxatives are to be started immediately.

An overdose of ANTICHOLIUM® can cause bradycardia, hypersalivation, vomiting, and generalized tonic-clonic seizures.

Patients should be closely monitored by ECG.

Adverse Reactions:

Like all medicines, ANTICHOLIUM® can cause side effects, although not everybody gets them.

System organ class | Frequency: Unknown
Immune system disorders | Hypersensitivity reactions
Endocrine disorders | Hypersalivation
Heart diseases | Changes of the heart rate (both bradycardia and tachycardia), sinoatrial block
Vascular diseases | Low blood pressure (hypotension)
Respiratory, thoracic and mediastinal disorders | Spasms of the respiratory tract (broncho spasms)
Gastrointestinal disorders | Nausea, vomiting
Skin and subcutaneous tissue disorders | Sweating

Usage in pregnancy:

Pregnancy and breast-feeding

Pregnancy:

There is no experience with the use of ANTICHOLIUM® in pregnant women.

Physostigmine, the active substance contained in ANTICHOLIUM®, passes into the placenta. Animal studies are insufficient with respect to effects on pregnancy, embryonal/foetal development, birth and postnatal development. The potential risk for humans is unknown.

For this reason, ANTICHOLIUM® may only be administered to pregnant women if deemed absolutely necessary by the attending doctor.

LACTATION

Breast-feeding:

There is no experience with the use of ANTICHOLIUM® during breastfeeding.

It is not known whether physostigmine, the active substance contained in ANTICHOLIUM®, is excreted in human breast milk. For this reason, ANTICHOLIUM® may only be used during breastfeeding if deemed absolutely necessary by the attending doctor.

Storage Conditions:

Store this medicine protected from light in the outer packaging, not above 25°C.
In undamaged container: 3 years
The infusion solution should be used immediately after preparation.
Keep this medicine out of the reach of children.
Do not use this medicine after the expiry date which is stated on the carton/label after EXP. The expiry date refers to the last day of that month.

How Supplied:

ANTICHOLIUM® is a clear, colorless to slightly reddish solution in glass ampules.

Pack containing 5 ampules with 5 ml.

Manufacturer:

Dr. Franz Köhler Chemie GmbH

Werner-von-Siemens-Str. 14-28

D-64625 Bensheim

Germany

Last revision of the text:

July 2023

PRINCIPAL DISPLAY PANEL - 5 x 5 mL Carton

ANTICHOLIUM®

2 mg/5 mL (0.4 mg/mL) solution for injection
Active substance: physostigmine salicylate

5 mL solution for injection contain:
2.0 mg physostigmine salicylate (0.4 mg/mL)
Sodium edetate (Ph. Eur.), sodium hydroxide for pH adjustment,
hydrochloric acid for pH adjustment, water for injections

DR. F. KÖHLER CHEMIE
Arzneimittel

PRINCIPAL DISPLAY PANEL - 5 mL Ampule

5 mL solution for injection

ANTICHOLIUM®

2 mg/5 mL (0.4 mg/mL)
solution for injection
Active substance:
physostigmine salicylate
For I.V. use

DR. FRANZ KÖHLER CHEMIE GMBH
Werner-von-Siemens-Str. 14-28
D-64625 Bensheim, Germany

LOT: / EXP.:

V01/05.23